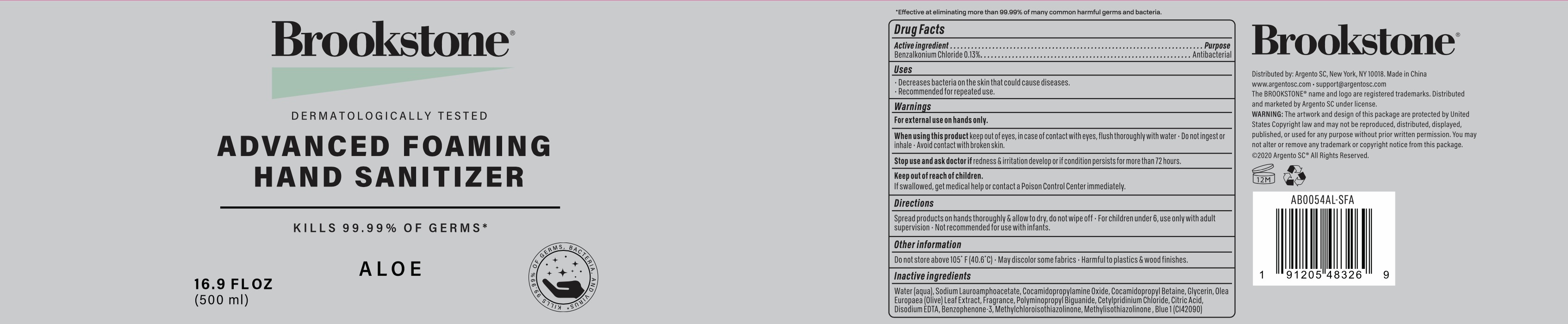 DRUG LABEL: Brookstone Aloe Advanced Foaming Hand Sanitizer
NDC: 77731-089 | Form: SOLUTION
Manufacturer: Argento sc by sicura inc.
Category: otc | Type: HUMAN OTC DRUG LABEL
Date: 20200917

ACTIVE INGREDIENTS: BENZALKONIUM CHLORIDE 0.13 g/100 mL
INACTIVE INGREDIENTS: SODIUM LAUROAMPHOACETATE; COCAMIDOPROPYLAMINE OXIDE; WATER; COCAMIDOPROPYL BETAINE; GLYCERIN; OLEA EUROPAEA LEAF; CETYLPYRIDINIUM CHLORIDE; CITRIC ACID MONOHYDRATE; DISODIUM HEDTA; BENZOPHENONE; METHYLCHLOROISOTHIAZOLINONE; METHYLISOTHIAZOLINONE; FD&C BLUE NO. 1

77731-089/AB0054AL-SFA foaming

Active Ingredient(s)

Benzalkonium Chloride 0.13%

Purpose:

Antibacterial

Use

Decreases bacteria on skin that could cause diseases

Recommended for repeated use

Warnings

For external use on hands only.

When using this product, keep out of eyes. In case of contact with eyes, flush thoroughly with water

Do not ingest or inhale

Avoid contact with broken skin

Stop use and ask a doctor

if irrigation and redness develop or if condition persists for more than 72 hours

Keep out of reach of children

If swallowed, get medical help or contact a Poison Control Center immediately

Directions

- Spread product on hands thoroughly and allow to dry, do not wipe off
- For children under 6, use only under adult supervision
- Not recommended for use with infants

Other information

Do not store above 105F (40.6C)

May discolor some fabrics

Harmful to plastics and wood finished

Inactive ingredients

Water, Sodium lauroamphoacetate, Cocamidopropylamine oxide, Cocamidopropyl betaine, Glycerin, Olea europaea (olive) leaf extract, Polyminopropyl biguanide, Citric acid, Disodium EDTA, Benzophenone-3, Methylchloroisothiazolinone, Methylisothiazolinone, Fragrance, Cetylpyridinium chloride, Blue 1 (CI42090)